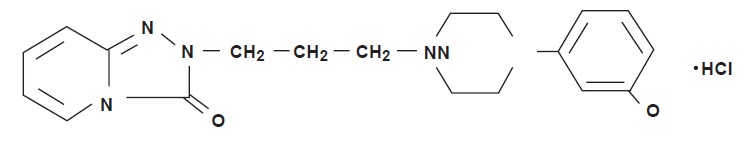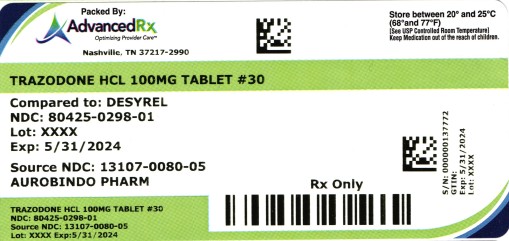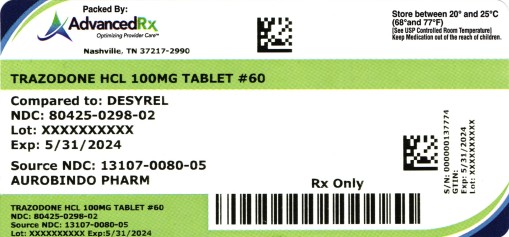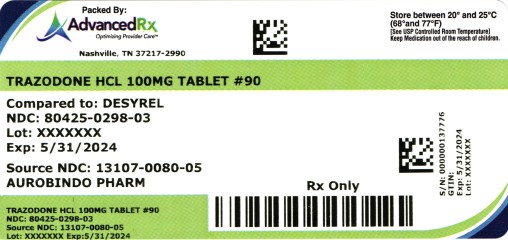 DRUG LABEL: Trazodone Hydrochloride
NDC: 80425-0298 | Form: TABLET
Manufacturer: Advanced Rx Pharmacy of Tennessee, LLC
Category: prescription | Type: HUMAN PRESCRIPTION DRUG LABEL
Date: 20260105

ACTIVE INGREDIENTS: TRAZODONE HYDROCHLORIDE 100 mg/1 1

Trazodone HCL Tablet

WARNING: SUICIDAL THOUGHTS AND BEHAVIORS

Antidepressants increased the risk of suicidal thoughts and behaviors in pediatric and young adult patients in short-term studies. Closely monitor all antidepressant-treated patients for clinical worsening, and for emergence of suicidal thoughts and behaviors [see WARNINGS AND PRECAUTIONS (5.1)]. Trazodone Hydrochloride Tablets are not approved for use in pediatric patients [see USE IN SPECIFIC POPULATIONS (8.4)].

1. Indications and Usage

Trazodone Hydrochloride Tablets are indicated for the treatment of major depressive disorder (MDD) in adults.

2. Dosage and Administration

2.1 Dose Selection

An initial dose of 150 mg/day in divided doses is suggested. The dosage should be initiated at a low-dose and increased gradually, noting the clinical response and any evidence of intolerance. Occurrence of drowsiness may require the administration of a major portion of the daily dose at bedtime or a reduction of dosage.
The dose may be increased by 50 mg/day every 3 to 4 days. The maximum dose for outpatients usually should not exceed 400 mg/day in divided doses.
Inpatients (i.e., more severely depressed patients) may be given up to but not in excess of 600 mg/day in divided doses.
Once an adequate response has been achieved, dosage may be gradually reduced, with subsequent adjustment depending on therapeutic response.

2.2 Important Administration Instructions

Trazodone Hydrochloride Tablets can be swallowed whole or administered as a half tablet by breaking the tablet along the score line. Trazodone Hydrochloride Tablets should be taken shortly after a meal or light snack.

2.3 Screen for Bipolar Disorder Prior to Starting Trazodone Hydrochloride Tablets

Prior to initiating treatment with Trazodone Hydrochloride Tablets or another antidepressant, screen patients for a personal or family history of bipolar disorder, mania, or hypomania [see WARNINGS AND PRECAUTIONS (5.7)].

2.4 Switching to or from Monoamine Oxidase Inhibitor Antidepressant

At least 14 days must elapse between discontinuation of a monoamine oxidase inhibitor (MAOI) antidepressant and initiation of Trazodone Hydrochloride Tablets. In addition, at least 14 days must elapse after stopping Trazodone Hydrochloride Tablets before starting an MAOI antidepressant [see CONTRAINDICATIONS (4), WARNINGS AND PRECAUTIONS (5.2)].

2.5 Dosage Recommendations for Concomitant Use with Strong CYP3A4 Inhibitors or Inducers

Coadministration with Strong CYP3A4 Inhibitors
Consider reducing Trazodone Hydrochloride Tablets dose based on tolerability when Trazodone Hydrochloride Tablets are coadministered with a strong CYP3A4 inhibitor [see DRUG INTERACTIONS (7.1)].

Coadministration with Strong CYP3A4 Inducers
Consider increasing Trazodone Hydrochloride Tablets dose based on therapeutic response when Trazodone Hydrochloride Tablets are coadministered with a strong CYP3A4 inducer [see DRUG INTERACTIONS (7.1)].

2.6 Discontinuation of Treatment with Trazodone Hydrochloride Tablets

Adverse reactions may occur upon discontinuation of Trazodone Hydrochloride Tablets [See WARNINGS AND PRECAUTIONS (5.8)]. Gradually reduce the dosage rather than stopping Trazodone Hydrochloride Tablets abruptly whenever possible.

3. Dosage Forms and Strengths

Trazodone hydrochloride tablets USP are available in the following strengths:

50 mg: White to off-white, round, biconvex, uncoated tablets, debossed with ‘J’ and ‘43’ on either side of scoreline (functional) on one side and plain on the other side.
100 mg: White to off-white, round, biconvex, uncoated tablets, debossed with ‘J’ and ‘44’ on either side of scoreline (functional) on one side and plain on the other side.
150 mg: White to off-white, oval, flat faced, beveled-edge, uncoated tablets with one side scored (functional) with full bisect debossed with ‘J’ and ‘45’ on either side and having two partial trisect on one side and plain on the other side.
300 mg: White to off-white, oval, flat faced, beveled-edge, uncoated tablets with one side scored (functional) with full bisect debossed with ‘J’ and ‘46’ on either side and having two partial trisect on one side and plain on the other side.

4. Contraindications

Trazodone Hydrochloride Tablets are contraindicated in:

Patients taking, or within 14 days of stopping, monoamine oxidase inhibitors (MAOIs), including MAOIs such as linezolid or intravenous methylene blue, because of an increased risk of serotonin syndrome [see WARNINGS AND PRECAUTIONS (5.2), DRUG INTERACTIONS (7.1)].

5. Warnings and Precautions

5.1 Suicidal Thoughts and Behaviors in Pediatric and Young Adult Patients

In pooled analyses of placebo-controlled trials of antidepressant drugs (SSRIs and other antidepressant classes) that included approximately 77,000 adult patients and over 4,400 pediatric patients, the incidence of suicidal thoughts and behaviors in pediatric and young adult patients was greater in antidepressant-treated patients than in placebo-treated patients. The drug-placebo differences in the number of cases of suicidal thoughts and behaviors per 1000 patients treated are provided in Table 1.

No suicides occurred in any of the pediatric studies. There were suicides in the adult studies, but the number was not sufficient to reach any conclusion about antidepressant drug effect on suicide.

Table 1: Risk Differences of the Number of Cases of Suicidal Thoughts or Behaviors in the Pooled Placebo-Controlled

Age Range (years) | Drug-Placebo Differencein Number of Patients of Suicidal Thoughts or Behaviors per 1000 Patients Treated
 | Increases Compared to Placebo
<18 | 14 additional patients
18-24 | 5 additional patients
 | Decreases Compared to Placebo
25-64 | 1 fewer patient
≥65 | 6 fewer patients

It is unknown whether the risk of suicidal thoughts and behaviors in pediatric and young adult patients extends to longer-term use, i.e., beyond four months. However, there is substantial evidence from placebo-controlled maintenance trials in adults with MDD that antidepressants delay the recurrence of depression.

Monitor all antidepressant-treated patients for clinical worsening and emergence of suicidal thoughts and behaviors, especially during the initial few months of drug therapy and at times of dosage changes. Counsel family members or caregivers of patients to monitor for changes in behavior and to alert the healthcare provider. Consider changing the therapeutic regimen, including possibly discontinuing Trazodone Hydrochloride Tablets, in patients whose depression is persistently worse, or who are experiencing emergent suicidal thoughts or behaviors.

5.2 Serotonin Syndrome

Serotonin-norepinephrine reuptake inhibitors (SNRIs) and SSRIs, including Trazodone Hydrochloride Tablets, can precipitate serotonin syndrome, a potentially life-threatening condition. The risk is increased with concomitant use of other serotonergic drugs (including triptans, tricyclic antidepressants, fentanyl, lithium, tramadol, tryptophan, buspirone, and St. John’s Wort) and with drugs that impair metabolism of serotonin, i.e., MAOIs [see CONTRAINDICATIONS (4), DRUG INTERACTIONS (7.1)]. Serotonin syndrome can also occur when these drugs are used alone.

Serotonin syndrome signs and symptoms may include mental status changes (e.g., agitation, hallucinations, delirium, and coma), autonomic instability (e.g., tachycardia, labile blood pressure, dizziness, diaphoresis, flushing, hyperthermia), neuromuscular symptoms (e.g., tremor, rigidity, myoclonus, hyperreflexia, incoordination), seizures, and gastrointestinal symptoms (e.g., nausea, vomiting, diarrhea).

The concomitant use of Trazodone Hydrochloride Tablets with MAOIs is contraindicated. In addition, do not initiate Trazodone Hydrochloride Tablets in a patient being treated with MAOIs such as linezolid or intravenous methylene blue. No reports involved the administration of methylene blue by other routes (such as oral tablets or local tissue injection). If it is necessary to initiate treatment with an MAOI such as linezolid or intravenous methylene blue in a patient taking Trazodone Hydrochloride Tablets, discontinue Trazodone Hydrochloride Tablets before initiating treatment with the MAOI [see CONTRAINDICATIONS (4), DRUG INTERACTIONS (7.1)].

Monitor all patients taking Trazodone Hydrochloride Tablets for the emergence of serotonin syndrome. Discontinue treatment with Trazodone Hydrochloride Tablets and any concomitant serotonergic agents immediately if the above symptoms occur, and initiate supportive symptomatic treatment. If concomitant use of Trazodone Hydrochloride Tablets with other serotonergic drugs is clinically warranted, inform patients of the increased risk for serotonin syndrome and monitor for symptoms.

5.3 Cardiac Arrhythmias

Clinical studies indicate that trazodone hydrochloride may be arrhythmogenic in patients with preexisting cardiac disease. Arrhythmias identified include isolated PVCs, ventricular couplets, tachycardia with syncope, and torsade de pointes. Post marketing events, including torsade de pointes have been reported at doses of 100 mg or less with the immediate-release form of Trazodone Hydrochloride Tablets. Trazodone Hydrochloride Tablets should also be avoided in patients with a history of cardiac arrhythmias, as well as other circumstances that may increase the risk of the occurrence of torsade de pointes and/or sudden death, including symptomatic bradycardia, hypokalemia or hypomagnesemia, and the presence of congenital prolongation of the QT interval. Trazodone Hydrochloride Tablets are not recommended for use during the initial recovery phase of myocardial infarction. Caution should be used when administering Trazodone Hydrochloride Tablets to patients with cardiac disease and such patients should be closely monitored, since antidepressant drugs (including Trazodone Hydrochloride Tablets) may cause cardiac arrhythmias [see ADVERSE REACTIONS (6.2)].

Trazodone Hydrochloride Tablets prolongs the QT/QTc interval. The use of Trazodone Hydrochloride Tablets should be avoided in patients with known QT prolongation or in combination with other drugs that are inhibitors of CYP3A4 (e.g., itraconazole, clarithromycin, voriconazole), or known to prolong QT interval including Class 1A antiarrhythmics (e.g., quinidine, procainamide) or Class 3 antiarrhythmics (e.g., amiodarone, sotalol), certain antipsychotic medications (e.g., ziprasidone, chlorpromazine, thioridazine), and certain antibiotics (e.g., gatifloxacin). Concomitant administration of drugs may increase the risk of cardiac arrhythmia [see DRUG INTERACTIONS (7.1)].

5.4 Orthostatic Hypotension and Syncope

Hypotension, including orthostatic hypotension and syncope has been reported in patients receiving trazodone hydrochloride. Concomitant use with an antihypertensive may require a reduction in the dose of the antihypertensive drug.

5.5 Increased Risk of Bleeding

Drugs that interfere with serotonin reuptake inhibition, including Trazodone Hydrochloride Tablets, increase the risk of bleeding events. Concomitant use of aspirin, nonsteroidal anti-inflammatory drugs (NSAIDS), other antiplatelet drugs, warfarin, and other anticoagulants may add to this risk.

Case reports and epidemiological studies (case-control and cohort design) have demonstrated an association between use of drugs that interfere with serotonin reuptake and the occurrence of gastrointestinal bleeding. Bleeding events related to drugs that interfere with serotonin reuptake have ranged from ecchymosis, hematoma, epistaxis, and petechiae to life-threatening hemorrhages.
Inform patients about the risk of bleeding associated with the concomitant use of Trazodone Hydrochloride Tablets and antiplatelet agents or anticoagulants. For patients taking warfarin, carefully monitor coagulation indices when initiating, titrating, or discontinuing Trazodone Hydrochloride Tablets.

5.6 Priapism

Cases of priapism (painful erections greater than 6 hours in duration) have been reported in men receiving Trazodone Hydrochloride Tablets. Priapism, if not treated promptly, can result in irreversible damage to the erectile tissue. Men who have an erection lasting greater than 4 hours, whether painful or not, should immediately discontinue the drug and seek emergency medical attention [see ADVERSE REACTIONS (6.2), OVERDOSAGE (10)].

Trazodone Hydrochloride Tablets should be used with caution in men who have conditions that might predispose them to priapism (e.g., sickle cell anemia, multiple myeloma, or leukemia), or in men with anatomical deformation of the penis (e.g., angulation, cavernosal fibrosis, or Peyronie’s disease).

5.7 Activation of Mania or Hypomania

In patients with bipolar disorder, treating a depressive episode with Trazodone Hydrochloride Tablets or another antidepressant may precipitate a mixed/manic episode. Activation of mania/hypomania has been reported in a small proportion of patients with major affective disorder who were treated with antidepressants. Prior to initiating treatment with Trazodone Hydrochloride Tablets, screen patients for any personal or family history of bipolar disorder, mania, or hypomania [see DOSAGE AND ADMINISTRATION (2.3)].

5.8 Discontinuation Syndrome

Adverse reactions after discontinuation of serotonergic antidepressants, particularly after abrupt discontinuation, include: nausea, sweating, dysphoric mood, irritability, agitation, dizziness, sensory disturbances (e.g., paresthesia, such as electric shock sensations), tremor, anxiety, confusion, headache, lethargy, emotional lability, insomnia, hypomania, tinnitus, and seizures. A gradual reduction in dosage rather than abrupt cessation is recommended whenever possible [See DOSAGE AND ADMINISTRATION (2.6)].

5.9 Potential for Cognitive and Motor Impairment

Trazodone Hydrochloride Tablets may cause somnolence or sedation and may impair the mental and/or physical ability required for the performance of potentially hazardous tasks. Patients should be cautioned about operating hazardous machinery, including automobiles, until they are reasonably certain that the drug treatment does not affect them adversely.

5.10 Angle-Closure Glaucoma

The pupillary dilation that occurs following use of many antidepressant drugs including Trazodone Hydrochloride Tablets may trigger an angle closure attack in a patient with anatomically narrow angles who does not have a patent iridectomy. Avoid use of antidepressants, including Trazodone Hydrochloride Tablets, in patients with untreated anatomically narrow angles.

5.11 Hyponatremia

Hyponatremia may occur as a result of treatment with SNRIs and SSRIs, including Trazodone Hydrochloride Tablets. Cases with serum sodium lower than 110 mmol/L have been reported. Signs and symptoms of hyponatremia include headache, difficulty concentrating, memory impairment, confusion, weakness, and unsteadiness, which can lead to falls. Signs and symptoms associated with more severe and/or acute cases have included hallucination, syncope, seizure, coma, respiratory arrest, and death. In many cases, this hyponatremia appears to be the result of the syndrome of inappropriate antidiuretic hormone secretion (SIADH).

In patients with symptomatic hyponatremia, discontinue Trazodone Hydrochloride Tablets and institute appropriate medical intervention. Elderly patients, patients taking diuretics, and those who are volume-depleted may be at greater risk of developing hyponatremia with SSRIs and SNRIs [see USE IN SPECIFIC POPULATIONS (8.5)].

6. Adverse Reactions

The following serious adverse reactions are described elsewhere in the labeling:

Suicidal Thoughts and Behavior in Children, Adolescents and Young Adults [see BOXED WARNING and WARNINGS AND PRECAUTIONS (5.1)]
Serotonin Syndrome [see WARNINGS AND PRECAUTIONS (5.2)]
Cardiac Arrythmias [see WARNINGS AND PRECAUTIONS (5.3)]
Orthostatic Hypotension and Syncope [see WARNINGS AND PRECAUTIONS (5.4)]
Increased Risk of Bleeding [see WARNINGS AND PRECAUTIONS (5.5)]
Priapism [see WARNINGS AND PRECAUTIONS (5.6)]
Activation of Mania or Hypomania [see WARNINGS AND PRECAUTIONS (5.7)]
Discontinuation Syndrome [see WARNINGS AND PRECAUTIONS (5.8)]
Potential for Cognitive and Motor Impairment [see WARNINGS AND PRECAUTIONS (5.9)]
Angle-Closure Glaucoma [see WARNINGS AND PRECAUTIONS (5.10)]
Hyponatremia [see WARNINGS AND PRECAUTIONS (5.11)]

6.1 Clinical Trials Experience

Because clinical trials are conducted under widely varying conditions, adverse reaction rates observed in the clinical trials of a drug cannot be directly compared to rates in the clinical trials of another drug and may not reflect the rates observed in practice.

Table 2: Common Adverse Reactions Occurring in ≥ 2% of Trazodone Hydrochloride Tablets-treated Patients and Greater than the Rate of Placebo-Treated Patients as Observed in Controlled Clinical Studies

Inpatients |  | Outpatients
 | Trazodone Hydrochloride Tablets N=142 | Placebo N=95 | Trazodone Hydrochloride Tablets N=157 | Placebo N=158
Allergic
Skin Condition/Edema | 3% | 1% | 7% | 1%
Autonomic
Blurred Vision | 6% | 4% | 15% | 4%
Constipation | 7% | 4% | 8% | 6%
Dry Mouth | 15% | 8% | 34% | 20%
Cardiovascular
Hypertension | 20% | 1% | 1% | *
Hypotension | 7% | 1% | 4% | 0
Syncope | 3% | 2% | 5% | 1%
CNS
Confusion | 5% | 0 | 6% | 8%
Decreased Concentration | 3% | 2% | 1% | 0
Disorientation | 2% | 0 | * | 0
Fatigue | 11% | 4% | 6% | 3%
Headache | 10% | 5% | 20% | 16%
Nervousness | 15% | 11% | 6% | 8%
Gastrointestinal
Abdominal/Gastric Disorder | 4% | 4% | 6% | 4%
Diarrhea | 0 | 1% | 5% | 1%
Nausea/Vomiting | 10% | 1% | 13% | 10%
Musculoskeletal
Aches/Pains | 6% | 3% | 5% | 3%
Neurological
Incoordination | 5% | 0 | 2% | *
Tremors | 3% | 1% | 5% | 4%
Other
Eyes Red/Tired/Itching | 3% | 0 | 0 | 0
Head Full-Heavy | 3% | 0 | 0 | 0
Malaise | 3% | 0 | 0 | 0
Nasal/Sinus Congestion | 3% | 0 | 6% | 3%
Weight Gain | 1% | 0 | 5% | 2%
Weight Loss | * | 3% | 6% | 3%

Other adverse reactions occurring at an incidence of <2% with the use of trazodone hydrochloride in the controlled clinical studies: akathisia, allergic reaction, anemia, chest pain, delayed urine flow, early menses, flatulence, hallucinations/delusions, hematuria, hypersalivation, hypomania, impaired memory, impaired speech, impotence, increased appetite, increased libido, increased urinary frequency, missed periods, muscle twitches, numbness, paresthesia, retrograde ejaculation, shortness of breath, and tachycardia/palpitations. Occasional sinus bradycardia has occurred in long-term studies.

6.2 Post marketing Experience

The following adverse reactions have been identified during post-approval use of Trazodone Hydrochloride Tablets. Because these reactions are reported voluntarily from a population of uncertain size, it is not always possible to estimate their frequency or establish a causal relationship to drug exposure:

Blood and lymphatic system disorders: hemolytic anemia, leukocytosis

Cardiac disorders: cardio spasm, congestive heart failure, conduction block, orthostatic hypotension and syncope, palpitations, bradycardia, atrial fibrillation, myocardial infarction, cardiac arrest, arrhythmia, ventricular ectopic activity, including ventricular tachycardia and QT prolongation. Prolonged QT interval, torsade de pointes, and ventricular tachycardia have been reported at doses of 100 mg per day or less [see WARNINGS AND PRECAUTIONS (5.3)].
Endocrine disorders: inappropriate ADH syndrome
Eye disorders: diplopia
Gastrointestinal disorders: increased salivation, nausea/vomiting
General disorders and administration site conditions: chills, edema, unexplained death, weakness
Hepatobiliary disorders: cholestasis, jaundice, hyperbilirubinemia, liver enzyme alterations
Investigations: increased amylase
Metabolism and nutrition disorders: methemoglobinemia
Nervous system disorders: aphasia, ataxia, cerebrovascular accident, extrapyramidal symptoms, grand mal seizures, paresthesia, tardive dyskinesia, vertigo
Psychiatric disorders: abnormal dreams, agitation, anxiety, hallucinations, insomnia, paranoid reaction, psychosis, stupor
Renal and urinary disorders: urinary incontinence, urinary retention
Reproductive system and breast disorders: breast enlargement or engorgement, clitorism, lactation, priapism [see WARNINGS AND PRECAUTIONS (5.6)]Respiratory, thoracic and mediastinal disorders: apnea
Skin and subcutaneous tissue disorders: alopecia, hirsutism, leukonychia, pruritus, psoriasis, rash, urticaria
Vascular disorders: vasodilation

7. Drug Interactions

7.1 Drugs Having Clinically Important Interactions with Trazodone Hydrochloride Tablets

Table 3: Clinically Important Drug Interactions with Trazodone Hydrochloride Tablets

Monoamine Oxidase Inhibitors (MAOIs)
ClinicalImpact: | The concomitant use of MAOIs and serotonergic drugs including Trazodone hydrochloride tablets increases the risk of serotonin syndrome.
Intervention: | Trazodone hydrochloride tablets are contraindicated in patients taking MAOIs, including MAOIs such as linezolid or intravenous methylene blue [seeCONTRAINDICATIONS(4),DOSAGEANDADMINISTRATION(2.3,2.4), and WARNINGS AND PRECAUTIONS(5.2)].
Examples: | isocarboxazid, moclobemide,phenelzine,selegiline, tranylcypromine
Other Serotonergic Drugs
ClinicalImpact: | The concomitant use of serotonergic drugs including Trazodone hydrochloride tablets and other serotonergic drugs increases the risk of serotonin syndrome.
Intervention: | Monitorpatientsfor signsandsymptoms of serotoninsyndrome,particularly duringTrazodone hydrochloride tabletsinitiation. Ifserotoninsyndromeoccurs,considerdiscontinuation of Trazodone hydrochloride tablets and/or concomitantserotonergicdrugs[seeWARNINGS AND PRECAUTIONS(5.2)].
Examples: | triptans,antidepressants(tricyclicandserotoninuptakeinhibitors),fentanyl,lithium,tramadol,tryptophan,buspirone,andSt.John's Wort
AntiplateletAgents and Anticoagulants
ClinicalImpact: | Serotoninreleaseby platelets playsanimportantrole in hemostasis. Theconcurrentuseof an antiplateletagent or anticoagulantwithTrazodone hydrochloride tablets may potentiatetherisk of bleeding.
Intervention: | Inform patients of the increased risk of bleeding with the concomitantuse of Trazodone hydrochloride tablets and antiplateletagents and anticoagulants. For patients taking warfarin,carefully monitor the internationalnormalizedratio(INR)wheninitiating or discontinuing Trazodone hydrochloride tablets[see WARNINGS AND PRECAUTIONS(5.5)].
Examples: | warfarin, rivaroxaban,dabigatran,clopidogrel
StrongCYP3A4Inhibitors
ClinicalImpact: | Theconcomitantuse of Trazodone hydrochloride tablets and strongCYP3A4inhibitors increased the exposureoftrazodonecomparedtotheuse of Trazodone hydrochloride tabletsalone.
Intervention: | If Trazodone hydrochloride tablets areusedwith a potentCYP3A4inhibitor,therisk of adversereactions,includingcardiac arrhythmias,may be increased and a lowerdose of Trazodone hydrochloride tablets should be considered[see DOSAGEANDADMINISTRATION (2.5), WARNINGSANDPRECAUTIONS(5.3)].
Examples: | itraconazole,ketoconazole,clarithromycin,indinavir
StrongCYP3A4Inducers
ClinicalImpact: | The concomitant use of Trazodone hydrochloride tablets and strongCYP3A4inducers decreased the exposure of trazodone compared to the use of Trazodone hydrochloride tablets alone.
Intervention: | Patients should be closely monitored to see if there is a need for an increased dose of Trazodone hydrochloride tabletswhentakingCYP3A4inducers[seeDosageandAdministration(2.5)].
Examples: | rifampin,carbamazepine,phenytoin,St.John’swort
DigoxinandPhenytoin
ClinicalImpact: | Digoxinand phenytoin are narrowtherapeutic index drugs. Concomitant use of Trazodone hydrochloride tabletscan increase digoxin or phenytoinconcentrations.
Intervention: | Measureserumdigoxinor phenytoinconcentrations beforeinitiatingconcomitantuse of Trazodone hydrochloride tablets.Continuemonitoring and reducedigoxin or phenytoindoseas necessary.
Examples: | digoxin, phenytoin
CentralNervousSystem(CNS)Depressants
ClinicalImpact: | Trazodone hydrochloride tabletsmay enhancethe responseCNSdepressants.
Intervention: | Patients shouldbe counseledthatTrazodone hydrochloride tablets mayenhancetheresponsetoalcohol,barbiturates, and other CNSdepressants.
Examples: | alcohol,barbiturates
QTIntervalProlongation
ClinicalImpact: | Concomitant use of drugs that prolong the QT interval may add to the QT effects of Trazodone hydrochloride tablets and increase the risk of cardiac arrhythmia.
Intervention | Avoid the use of Trazodone hydrochloride tablets in combination with other drugs known to prolongQTc[seeWARNINGS AND PRECAUTIONS(5.3)].
Examples: | Class 1A antiarrhythmics:quinidine,procainamide,disopyramide; Class 3 antiarrhythmics:amiodarone,sotalol; Antipsychotics:ziprasidone,chlorpromazine,thioridazine;Antibiotics:gatifloxacin

8. Use in Specific Populations

8.1 Pregnancy

Pregnancy Exposure Registry

There is a pregnancy exposure registry that monitors pregnancy outcomes in women exposed to antidepressants during pregnancy. Healthcare providers are encouraged to register patients by calling the National Pregnancy Registry for Antidepressants at 1-844-405- 6185 or visiting online at https://womensmentalhealth.org/clinical-and-research programs/pregnancy registry/antidepressants/

Risk Summary

Published prospective cohort studies, case series, and case reports over several decades with Trazodone Hydrochloride Tablets use in pregnant women have not identified any drug-associated risks of major birth defects, miscarriage, or adverse maternal or fetal outcomes (see Data). Trazodone hydrochloride has been shown to cause increased fetal resorption and other adverse effects on the fetus in the rat when given at dose levels approximately 7.3 to 11 times the maximum recommended human dose (MRHD) of 400 mg/day in adults on a mg/m2 basis. There was also an increase in congenital anomalies in the rabbit at approximately 7.3 to 22 times the MRHD on a mg/m2 basis (see Data).

The estimated background risk of major birth defects and miscarriage for the indicated population is unknown. All pregnancies have a background risk of birth defect, loss, or other adverse outcomes. In the U.S. general population, the estimated background risk of major birth defects and miscarriage in clinically recognized pregnancies is 2 to 4% and 15 to 20%, respectively.

Clinical Considerations

Disease-associated maternal and/or embryo fetal risk

A prospective, longitudinal study followed 201 pregnant women with a history of major depressive disorder who were euthymic and taking antidepressants at the beginning of pregnancy. The women who discontinued antidepressants during pregnancy were more likely to experience a relapse of major depression that women who continued antidepressants. Consider the risk of untreated depression when discontinuing or changing treatment with antidepressant medication during pregnancy and postpartum.

Data

Human Data

While available studies cannot definitively establish the absence of risk, published data from prospective cohort studies, case series, and case reports over several decades have not identified an association with trazodone use during pregnancy and major birth defects, miscarriage, or other adverse maternal or fetal outcomes. All available studies have methodological limitations, including small sample size and inconsistent comparator groups.

Animal Data

No teratogenic effects were observed when trazodone was given to pregnant rats and rabbits during the period of organogenesis at oral doses up to 450 mg/kg/day. This dose is 11 and 22 times, in rats and rabbits, respectively, the maximum recommended human dose (MRHD) of 400 mg/day in adults on a mg/m2 basis. Increased fetal resorption and other adverse effects on the fetus in rats at 7.3 to 11 times the MRHD and increase in congenital anomalies in rabbits at 7.3 to 22 times the MRHD on a mg/m2 basis were observed. No further details on these studies are available.

8.2 Lactation

Risk Summary

Data from published literature report the transfer of trazodone into human milk. There are no data on the effect of trazodone on milk production. Limited data from post marketing reports have not identified and association of adverse effects on the breastfed child.
The developmental and health benefits of breastfeeding should be considered along with the mother’s clinical need for Trazodone Hydrochloride Tablets and any potential adverse effects on the breastfed child from Trazodone Hydrochloride Tablets or from the underlying maternal condition.

8.4 Pediatric Use

Safety and effectiveness in the pediatric population have not been established. Antidepressants increased the risk of suicidal thoughts and behaviors in pediatric patients [see BOXED WARNING, WARNINGS AND PRECAUTIONS (5.1)].

8.5 Geriatric Use

Reported clinical literature and experience with trazodone has not identified differences in responses between elderly and younger patients. However, as experience in the elderly with trazodone hydrochloride is limited, it should be used with caution in geriatric patients.
Serotonergic antidepressants have been associated with cases of clinically significant hyponatremia in elderly patients, who may be at greater risk for this adverse reaction [see WARNINGS AND PRECAUTIONS (5.11)].

8.6 Renal Impairment

Trazodone has not been studied in patients with renal impairment. Trazodone should be used with caution in this population.

8.7 Hepatic Impairment

Trazodone has not been studied in patients with hepatic impairment. Trazodone should be used with caution in this population.

9. Drug Abuse and Dependence

9.1 Controlled Substance

Trazodone Hydrochloride Tablets are not a controlled substance.

9.2 Abuse

Although trazodone hydrochloride has not been systematically studied in preclinical or clinical studies for its potential for abuse, no indication of drug-seeking behavior was seen in the clinical studies with trazodone hydrochloride.

10. Overdosage

Death from overdose has occurred in patients ingesting Trazodone Hydrochloride Tablets and other CNS depressant drugs concurrently (alcohol; alcohol and chloral hydrate and diazepam; amobarbital; chlordiazepoxide; or meprobamate).

The most severe reactions reported to have occurred with overdose of Trazodone Hydrochloride Tablets alone have been priapism, respiratory arrest, seizures, and ECG changes, including QT prolongation. The reactions reported most frequently have been drowsiness and vomiting. Overdosage may cause an increase in incidence or severity of any of the reported adverse reactions.

There is no specific antidote for trazodone hydrochloride overdose. In managing overdosage, consider the possibility of multiple drug involvement. For current information on the management of poisoning or overdose, contact a poison control center (1-800-222-1222 or www.poison.org).

11. Description

Trazodone hydrochloride tablets for oral administration contain trazodone hydrochloride, a selective serotonin reuptake inhibitor and 5HT2 receptor antagonist. Trazodone hydrochloride is a triazolopyridine derivative designated as 2-[3-[4-(3-chlorophenyl)-1piperazinyl]propyl]-1,2,4-triazolo [4,3-a]pyridin-3(2H)-one hydrochloride. It is a white odorless crystalline powder which is freely soluble in water. The structural formula is represented as follows:

Molecular Formula: C19H22CIN5O • HCl

Molecular Weight: 408.33

Each tablet, for oral administration, contains 50 mg, 100 mg, 150 mg or 300 mg of trazodone hydrochloride, USP. In addition, each tablet contains the following inactive ingredients: colloidal silicon dioxide, magnesium stearate, microcrystalline cellulose, pregelatinized starch (physically modified corn (maize) starch), sodium lauryl sulfate, and sodium starch glycolate.

Meets USP Dissolution Test 2.

12. Clinical Pharamcology

12.1 Mechanism of Action

The mechanism of trazodone’s antidepressant action is not fully understood, but is thought to be related to its enhancement of serotonergic activity in the CNS. Trazodone is both a selective serotonin reuptake inhibitor (SSRI) and a 5HT2 receptor antagonist and the net result of this action on serotonergic transmission and its role in trazodone’s antidepressant effect is unknown.

12.2 Pharmacodynamics

Preclinical studies have shown that trazodone selectively inhibits neuronal reuptake of serotonin (Ki = 367 nM) and acts as an antagonist at 5-HT-2A (Ki = 35.6 nM) serotonin receptors. Trazodone is also an antagonist at several other monoaminergic receptors including 5-HT2B (Ki = 78.4 nM), 5-HT2C (Ki = 224 nM), α1A (Ki = 153 nM), α2C (Ki = 155 nM) receptors and it is a partial agonist at 5- HT1A (Ki = 118 nM) receptor.

Trazodone antagonizes alpha 1-adrenergic receptors, a property which may be associated with postural hypotension.

12.3 Pharmacokinetics

Absorption

In humans, trazodone hydrochloride is absorbed after oral administration without selective localization in any tissue. When trazodone hydrochloride is taken shortly after ingestion of food, there may be an increase in the amount of drug absorbed, a decrease in maximum concentration and a lengthening in the time to maximum concentration. Peak plasma levels occur approximately one hour after dosing when trazodone hydrochloride is taken on an empty stomach or 2 hours after dosing when taken with food.

Metabolism

In vitro studies in human liver microsomes show that trazodone is metabolized, via oxidative cleavage, to an active metabolite, m- chlorophenylpiperazine (mCPP) by CYP3A4. Other metabolic pathways that may be involved in the metabolism of trazodone have not been well characterized. Trazodone is extensively metabolized; less than 1% of an oral dose is excreted unchanged in the urine.

Elimination

In some patients trazodone may accumulate in the plasma.

Protein Binding

Trazodone is 89 to 95% protein bound in vitro at concentrations attained with therapeutic doses in humans.

13. Non Clinical Toxicology

13.1 Carcinogenesis, Mutagenesis, Impairment of Fertility

Carcinogenesis

No drug- or dose-related occurrence of carcinogenesis was evident in rats receiving trazodone in daily oral doses up to 7.3 times the maximum recommended human dose (MRHD) of 400 mg/day in adults on a mg/m2 basis.

Mutagenesis

No genotoxicity studies were conducted with trazodone.

Impairment of Fertility

Trazodone has no effect on fertility in rats at doses up to 7.3 times the MRHD in adults on a mg/m2 basis.

14. Clinical Studies

The efficacy and safety of trazodone hydrochloride were established from inpatient and outpatient trials of the trazodone immediate release formulation in the treatment of major depressive disorder.

16. How Supplied/Storage and Handling

Trazodone Hydrochloride Tablets, USP 100 mg are white to off-white, round, biconvex, uncoated tablets, debossed with ‘J’ and ‘44’ on either side of scoreline (functional) on one side and plain on the other side.

Bottles of 30 Tablets NDC: 80425-0298-01

Bottles of 60 Tablets NDC: 80425-0298-02

Bottles of 90 Tablets NDC: 80425-0298-03

Store at 20°C to 25°C (68°F to 77°F). Excursions permitted between 15ºC and 30ºC (59°F to 86ºF) [see USP Controlled Room Temperature]. Dispense with a child-resistant closure in a tight, light-resistant container.

17. Patient Counseling Information

Advise the patient to read the FDA-approved patient labeling (Medication Guide).

Suicidal Thoughts and Behaviors

Advise patients and caregivers to look for the emergence of suicidality, especially early during treatment and when the dosage is adjusted up or down and instruct them to report such symptoms to the healthcare provider [see Box Warning and Warnings and Precautions (5.1)].

Dosage and Administration

Advise patients that Trazodone Hydrochloride Tablets should be taken shortly after a meal or light snack. Advise patients regarding the importance of following dosage titration instructions [see Dosage and Administration (2)].

Serotonin Syndrome

Caution patients about the risk of serotonin syndrome, particularly with the concomitant use of Trazodone Hydrochloride Tablets with other serotonergic drugs including triptans, tricyclic antidepressants, fentanyl, lithium, tramadol, tryptophan, buspirone, St. John’s Wort, and with drugs that impair metabolism of serotonin (in particular, MAOIs, both those intended to treat psychiatric disorders and also others, such as linezolid). Patients should contact their health care provider or report to the emergency room if they experience signs or symptoms of serotonin syndrome [see Warnings and Precautions (5.2) and Drug Interactions (7)].

Activation of Mania/Hypomania

Advise patients and their caregivers to observe for signs of activation of mania/hypomania and instruct them to report such symptoms to the healthcare provider [seeWarnings and Precautions (5.7)].

Increased Risk of Bleeding

Inform patients about the concomitant use of Trazodone Hydrochloride Tablets with aspirin, NSAIDs, other antiplatelet drugs, warfarin, or other anticoagulants because the combined use of drugs that interfere with serotonin reuptake and these medications has been associated with an increased risk of bleeding. Advise them to inform their health care providers if they are taking or planning to take any prescription or over-the-counter medications that increase the risk of bleeding [see Warnings and Precautions (5.5)].

Discontinuation Syndrome

Advise patients not to abruptly discontinue Trazodone Hydrochloride Tablets and to discuss any tapering regimen with their healthcare provider. Adverse reactions can occur when Trazodone Hydrochloride Tablets are discontinued [see Warnings and Precautions (5.8)].

Concomitant Medications

Advise patients to inform their health care providers if they are taking, or plan to take any prescription or over-the-counter medications since there is a potential for interactions [see Drug Interactions (7.1)].

Pregnancy

Advise patients to notify their healthcare provider if they become pregnant or intend to become pregnant during therapy with Trazodone Hydrochloride Tablets. Advise patients that there is a pregnancy exposure registry that monitors pregnancy outcomes in women exposed to Trazodone Hydrochloride Tablets during pregnancy [see Use in Special Populations (8.1)].

Dispense with Medication Guide available at www.aurobindousa.com/medication-guides

Distributed by:
Aurobindo Pharma USA, Inc.
279 Princeton-Hightstown Road
East Windsor, NJ 08520
Manufactured by:
Aurobindo Pharma Limited
Hyderabad-500 032, India

Distributed by:

Advanced Rx Pharmacy of Tennessee, LLC

Issued: 06/2022

Medication Guide

Trazodone Hydrochloride Tablets, USP
(traz’ oh done hye’’ droeklor’ ide)

What is the most important information I should know about Trazodone Hydrochloride Tablets?
Antidepressant medicines, depression or other serious mental illnesses, and suicidal thoughts or actions: Talk to your healthcare provider about:

- All risks and benefits of treatment with antidepressant medicines
- All treatment choices for depression or other serious mental illnesses

1. Antidepressant medicines may increase suicidal thoughts or actions in some children, teenagers, and young adults within the first few months of treatment.

2. Depression and other serious mental illnesses are the most important causes of suicidal thoughts and actions.
Some people may have a higher risk of having suicidal thoughts or actions. These include people who have or have a family history of bipolar illness (also called manic-depressive illness) or suicidal thoughts or actions.
3. How can I watch for and try to prevent suicidal thoughts and actions?

- Pay close attention to any changes, especially sudden changes in mood, behaviors, thoughts, or feelings. This is very important when an antidepressant medicine is started or when the dose is changed.
- Call your healthcare provider right away to report new or sudden changes in mood, behavior, thoughts or feelings.
- Keep all follow-up visits with your healthcare provider as scheduled. Call your healthcare provider between visits as needed, especially if you are worried about symptoms.

Call a healthcare provider right away if you have any of the following symptoms, especially if they are new, worse, or worry you:

- Thoughts about suicide or dying
- Attempts to commit suicide
- New or worse depression
- New or worse anxiety
- Feeling very agitated or restless
- Panic attacks
- Trouble sleeping (insomnia)
- New or worse irritability
- Acting aggressive, being angry or violent
- Acting on dangerous impulses
- An extreme increase in activity and talking (mania)
- Other unusual changes in behavior or mood

What else do I need to know about antidepressant medicines?

- Never stop an antidepressant medicine without first talking to a healthcare provider. Stopping an antidepressant medicine suddenly can cause other symptoms.
- Antidepressants are medicines used to treat depression and other illnesses. It is important to discuss all the risks of treating depression and also the risks of not treating it. You should discuss all treatment choices with your healthcare provider, not just the use of antidepressants.
- Antidepressant medicines have other side effects. Talk to your healthcare provider about the side effects of your medicines.
- Antidepressant medicines can interact with other medicines. Know all of the medicines that you take. Keep a list of all medicines to show your healthcare provider. Do not start new medicines without first checking with your healthcare provider.

It is not known if Trazodone Hydrochloride Tablets are safe and effective in children.

What is Trazodone Hydrochloride Tablets?
Trazodone Hydrochloride Tablets are a prescription medicine used in adults to treat major depressive disorder (MDD). Trazodone Hydrochloride Tablets belongs to a class of medicines known as SSRIs (or selective serotonin reuptake inhibitors).

Do not take Trazodone Hydrochloride Tablets:

- If you take a monoamine oxidase inhibitor (MAOI). Ask your healthcare provider or pharmacist if you are not sure if you take an MAOI, including the antibiotic linezolid, and intravenous methylene blue.
- Do not take an MAOI within 2 weeks of stopping Trazodone Hydrochloride Tablets unless directed to do so by your healthcare provider.
- Do not start Trazodone Hydrochloride Tablets if you stopped taking an MAOI in the last 2 weeks unless directed to do so by your healthcare provider.

Before you take Trazodone Hydrochloride Tablets tell your healthcare provider about all of your medical conditions, including if you:

- have heart problems, including QT prolongation or a family history of it
- have ever had a heart attack
- have bipolar disorder
- have liver or kidney problems
- have other serious medical conditions
- are pregnant or plan to become pregnant. It is not known if Trazodone Hydrochloride Tablets will harm your unborn baby. Talk to your healthcare provider about the risk to your unborn baby if you take Trazodone Hydrochloride Tablets.
  - If you become pregnant during treatment with Trazodone Hydrochloride Tablets, talk to your healthcare provider about registering with the National Pregnancy Registry for Antidepressants. You can register by calling 1-844-405-6185.
- are breastfeeding or plan to breastfeed. Trazodone Hydrochloride Tablets passes into your breast milk. Talk to your healthcare provider about the best way to feed your baby if you take Trazodone Hydrochloride Tablets.
- have taken a Monoamine Oxidase Inhibitor (MAOI) or if you have stopped taking an MAOI in the last 2 weeks.

Tell your healthcare provider about all the medicines you take, including prescription and over-the-counter medicines, vitamins, and herbal supplements. Using Trazodone Hydrochloride Tablets with certain other medicines can affect each other causing serious side effects.
Especially tell your healthcare provider if you take:

- triptans used to treat migraine headache
- medicines used to treat mood, anxiety, psychotic or thought disorders, including tricyclics, lithium, SSRIs, SNRIs, buspirone, or antipsychotics
- tramadol
- over-the-counter supplements such as tryptophan or St. John’s Wort
- nonsteroidal anti-inflammatory drugs (NSAIDS)
- aspirin
- warfarin (Coumadin, Jantoven)
- phenytoin (Mesantoin)
- diuretics

Know the medicines you take. Keep a list of them and show it to your healthcare provider and pharmacist when you get a new medicine.

How should I take Trazodone Hydrochloride Tablets?

- Take Trazodone Hydrochloride Tablets exactly as your healthcare provider tells you.
- Trazodone Hydrochloride Tablets should be taken shortly after a meal or light snack.
- If you feel drowsy after taking Trazodone Hydrochloride Tablets, talk to your healthcare provider. Your healthcare provider may change your dose or the time of day you take your Trazodone Hydrochloride Tablets.
- Do not stop taking Trazodone Hydrochloride Tablets without talking to your healthcare provider.
- Trazodone Hydrochloride Tablets should be swallowed whole or broken in half along the score line. Do not chew or crush Trazodone Hydrochloride Tablets. Tell your healthcare provider if you cannot swallow trazodone either whole or as a half tablet.
- If you take too much Trazodone Hydrochloride Tablets, call your healthcare provider, your Poison Control Center at 1-800-222-1222, or go to the nearest emergency room right away.

What should I avoid while taking Trazodone Hydrochloride Tablets?

- Do not drive, operate heavy machinery, or do other dangerous activities until you know how Trazodone Hydrochloride Tablets affects you. Trazodone Hydrochloride Tablets can slow your thinking and motor skills.
- Do not drink alcohol or take other medicines that make you sleepy or dizzy while taking Trazodone Hydrochloride Tablets until you talk with your healthcare provider. Trazodone Hydrochloride Tablets may make your sleepiness or dizziness worse if you take it with alcohol or other medicines that cause sleepiness or dizziness.

What are the possible side effects of Trazodone Hydrochloride Tablets?
Trazodone Hydrochloride Tablets can cause serious side effects or death, including:

- See “What is the most important information I should know about Trazodone Hydrochloride Tablets?”
- Serotonin syndrome. Symptoms of serotonin syndrome include: agitation, hallucinations, and problems with coordination, fast heartbeat, tight muscles, trouble walking, sweating, fever, nausea, vomiting, and diarrhea.
- Irregular or fast heartbeat or faint (QT prolongation)
- Low blood pressure. You feel dizzy or faint when you change positions (go from sitting to standing)
- Unusual bruising or bleeding
- Erection lasting for more than 6 hours (priapism)
- Feeling high or in a very good mood, then becoming irritable, or having too much energy, feeling like you have to keep talking or do not sleep (mania).
- Withdrawal symptoms. Symptoms of withdrawal can include anxiety, agitation, and sleep problems. Do not stop taking Trazodone Hydrochloride Tablets without talking to your healthcare provider.

• Visual problems.

- eye pain
- changes in vision
- swelling or redness in or around the eye

Only some people are at risk for these problems. You may want to undergo an eye examination to see if you are at risk and receive preventative treatment if you are.

- Low sodium in your blood (hyponatremia). Symptoms of hyponatremia include: headache, feeling weak, feeling confused, trouble concentrating, memory problems and feeling unsteady when you walk.

Get medical help right away, if you have any of the symptoms listed above.
The most common side effects of Trazodone Hydrochloride Tablets include:

- swelling
- blurred vision
- dizziness
- sleepiness
- tiredness
- diarrhea
- stuffy nose
- weight loss

These are not all the possible side effects of Trazodone Hydrochloride Tablets. Call your doctor for medical advice about side effects. You may report side effects to FDA at 1-800-FDA-1088.

How should I store Trazodone Hydrochloride Tablets?

- Store Trazodone Hydrochloride Tablets at room temperature between 68°F to 77°F (20°C to 25°C).
- Keep in tight container
- Keep out of the light
- Safely throw away medicine that is out of date or no longer needed.

Keep Trazodone Hydrochloride Tablets and all medicines out of the reach of children.

General information about the safe and effective use of Trazodone Hydrochloride Tablets.
Medicines are sometimes prescribed for purposes other than those listed in a Medication Guide. Do not use Trazodone Hydrochloride Tablets for a condition for which it was not prescribed. Do not give Trazodone Hydrochloride Tablets to other people, even if they have the same symptoms that you have. It may harm them. You can ask your pharmacist or healthcare provider for information about Trazodone Hydrochloride Tablets that is written for health professionals.

What are the ingredients in Trazodone Hydrochloride Tablets?
Active ingredient: Trazodone Hydrochloride, USP
Inactive ingredients: colloidal silicon dioxide, magnesium stearate, microcrystalline cellulose, pregelatinized starch (physically modified corn (maize) starch), sodium lauryl sulfate, and sodium starch glycolate.
Dispense with Medication Guide available at www.aurobindousa.com/medication-guides
Distributed by:
Aurobindo Pharma USA, Inc.
279 Princeton-Hightstown Road
East Windsor, NJ 08520
Manufactured by:
Aurobindo Pharma Limited
Hyderabad-500 032, India
Issued: 06/2022